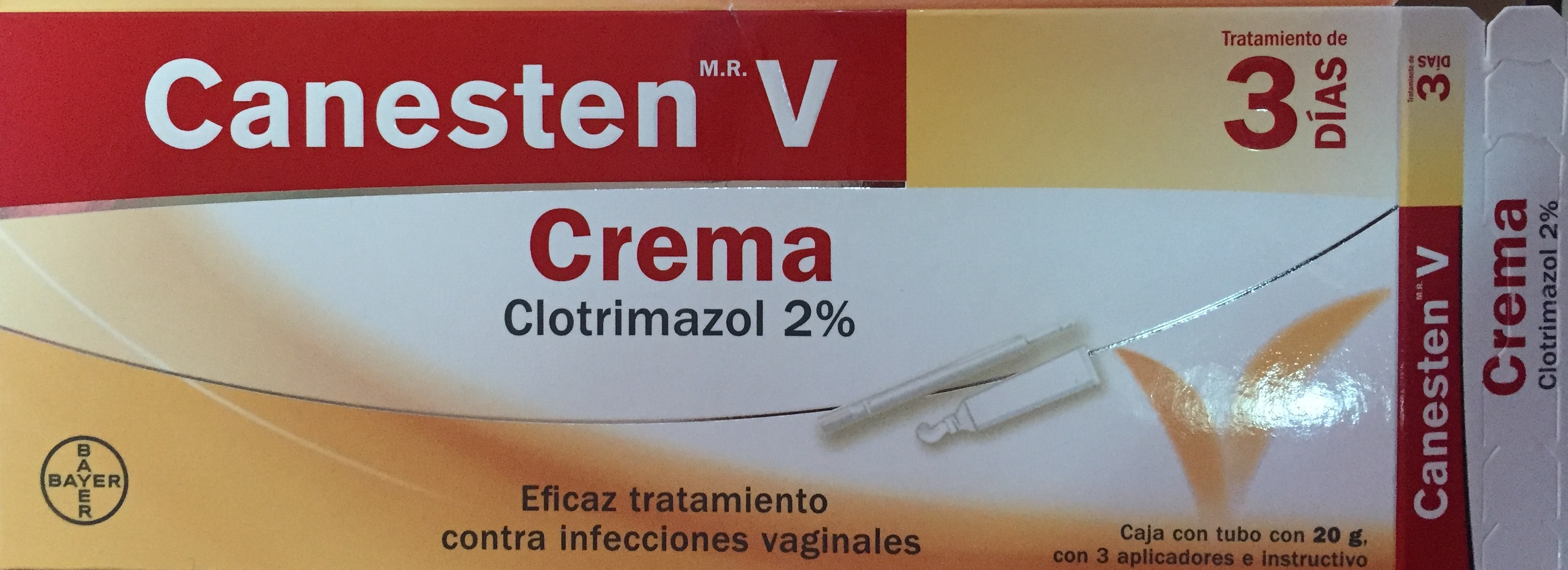 DRUG LABEL: CANESTEN
NDC: 69772-200 | Form: CREAM
Manufacturer: GENESIS IMPORTS & EXPORTS LLC
Category: otc | Type: HUMAN OTC DRUG LABEL
Date: 20171228

ACTIVE INGREDIENTS: CLOTRIMAZOLE 2 g/100 g
INACTIVE INGREDIENTS: POLYSORBATE 60; BENZYL ALCOHOL; CETOSTEARYL ALCOHOL; CETYL ESTERS WAX; OCTYLDODECANOL; WATER; SORBITAN MONOSTEARATE

ACTIVE INGREDIENTS

CLOTRIMAZOLE 2%

PURPOSE

Vaginal Antifungal

USE

- TREATS VAGINAL YEAST INFECTIONS
- RELIEVES EXTERNAL ITCHING AND IRRITATION DUE TO A VAGINAL YEAST INFECTION

WARNINGS

FOR VAGINAL USE ONLY

DPO NOT USE IF YOU HAVE NEVER HAD VAGINAL YEAST INFECTION DIAGNOSED BY

A DOCTOR

Ask A Doctor before if you have

- Vaginal itching and discomfort for the first time
- lower abdominal, back or shoulder pain, fever,chillis, nausea, vomiying, or foul-smelling vaginal discharge. You may have a more serious condition.
- Vaginal yeast infections often (such as once a mont h or 3 in 6 month). You can be pregnat or have a serious underlying medical cause for your sy mptoms, including, inclyding diabetes or a weakened immune system.
- been exposed to the human immunodefiency virus (HIV) that causes AIDS

STOP USE A ND ASK A DOCTOR IF

- SYMPTOMS DO NOT GE T BETTER IN 3 DAYS
- SYMPTOMS LAST MORE THAN 7 DAYS
- DO YOU GET A RUSH OR HIVE, ABDOMINAL PAIN, FEVER , CHILLS, NAUSEA, VOMITING, OR A FOU L-SMELLING VAGINA L DISCHARGE .

PREGNANCY OR BREAST FEEDING

IF PREGNANT OR BREAST-FEEDING, ASK A HEALTH PROFESSIONAL BEFORE USE

KEEP OUT OF REACH OF CHILDREN

KEEP OUT OF CHILDREN, IF SWALLOWED, GET MEDICAL HELP OR CONTACT A POISON CONTROL CENTER RIGHT A WAY

DOSAGE AND ADMINISTRATION

DIRECTION

- BEFORE US EINF THIS PRODUCT READ THE ENCLOSED EDUCATIONAL BROCHURE FOR COMPLETE DIRECTIONS AND INFORMATION
  - ADULTS AND CHILDREN 12 YEARS OF AGE AND OVER:

1. VAGINA CREAM:INSERT ONE APPLICATOTFUL OF CREAM INTO TEH VAGINA AT BEDTIME FOR 3 DAYS IN A ROW. TROW APPLICATOR AWAY AFTER USE.
2. EXTERNAL USE: CREAM :USE THE SAME TUBE OF CREAM IF YOU HAVE ICHING AND IRRITATION ON THE SKIN OUTSIDE THE VAGINA. SQUEEZE SMALL AMOUNT OF CREAM ONTO YOUR FINGERTIP. APPLY TO ICHY, IRRITATED SKIN OUTSIDE THE VAGINA.. USE 2 TIMES DAULY FOR UP TP 7 DAY AS NEEDED
3. CHILDREN UNDER 12 YEARS OF AGE : ASK A DOCTOR

OTHER INFORMATION

- TO OPEN: UNSCREW CAP, USE POINED END ON CAP TO PUNCTURE SEAL

DO NOT USE IF CARTON IS OPENED

- SAFETY SEALED: THE TUBE OPENING SHOULD BE SEALED. IF THE SEAL HAS BEEN PUNCTURED OR IS NOT BISIBLE, DO NOY USE THE PRODUCT
- STORE BETWEEN 20 TO 25 C (68 TO 77 F)
- SEE FLAP OF CARTON OR CRIMP OF TUBE DOR LOT NUMBER AND EXPIRATION DATE

INACTIVE INGREDIENT

Banzyl alcohol

Cetostearyl alcohol

cetyl esters wax

octydocanol

polysorbate 60

water

sorbitan monostearate